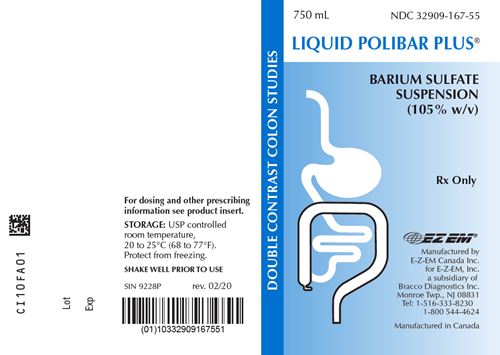 DRUG LABEL: Liquid Polibar Plus
NDC: 32909-167 | Form: SUSPENSION
Manufacturer: E-Z-EM Canada Inc
Category: prescription | Type: HUMAN PRESCRIPTION DRUG LABEL
Date: 20251218

ACTIVE INGREDIENTS: barium sulfate 1.05 g/1 mL
INACTIVE INGREDIENTS: acacia; anhydrous citric acid; dimethicone 350; dimethicone 1000; hydrochloric acid; polysorbate 80; potassium chloride; potassium sorbate; water; saccharin sodium; silicon dioxide; sodium benzoate; carrageenan; trisodium citrate dihydrate; sorbitol; xanthan gum

LIQUID POLIBAR PLUS®
BARIUM SULFATE SUSPENSION
(105% w/v, 58% w/w)

DESCRIPTION

LIQUID POLIBAR PLUS® Barium Sulfate Suspension (105% w/v, 58% w/w) is a barium sulfate suspension for oral and rectal administration. Each 100 mL contains 105 g barium sulfate. Barium sulfate, due to its high molecular density is opaque to x-rays and, therefore, acts as a positive contrast agent for radiographic studies. The active ingredient is barium sulfate and its structural formula is BaSO4. Barium sulfate occurs as a fine, white, odorless, tasteless, bulky powder which is free from grittiness. Its aqueous suspensions are neutral to litmus. It is practically insoluble in water, solutions of acids and alkalies, and organic solvents.

Inactive Ingredients

acacia, citric acid, hydrochloric acid, natural and artificial vanilla flavor, polysorbate 80, potassium chloride, potassium sorbate, purified water, saccharin sodium, simethicone emulsion, sodium benzoate, sodium carrageenan, sodium citrate, sorbitol solution and xanthan gum.

CLINICAL PHARMACOLOGY

Barium sulfate, due to its high molecular density is opaque to x-rays and, therefore, acts as a positive contrast agent for radiographic studies. Barium sulfate is biologically inert and, therefore, is not absorbed or metabolized by the body, and is eliminated unchanged from the body.

INDICATIONS AND USAGE

For radiography of the gastrointestinal tract.

CONTRAINDICATIONS

Oral Administration

This product should not be used in patients with known gastric or intestinal perforation or hypersensitivity to barium sulfate products.

Rectal Administration

This product should not be used in patients with known intestinal perforation or hypersensitivity to barium sulfate products.

WARNINGS

Rarely, severe allergic reactions of an anaphylactoid nature, have been reported following administration of barium sulfate contrast agents. Appropriately trained personnel and facilities should be available for emergency treatment of severe reactions and should remain available for at least 30 to 60 minutes following administration, since delayed reactions can occur.

PRECAUTIONS

General

Diagnostic procedures which involve the use of radiopaque contrast agents should be carried out under the direction of personnel with the requisite training and with a thorough knowledge of the particular procedure to be performed. A history of bronchial asthma, atopy, as evidenced by hay fever and eczema, or a previous reaction to a contrast agent, warrant special attention. Caution should be exercised with the use of radiopaque media in severely debilitated patients and in those with marked hypertension or advanced cardiac disease.

Ingestion of this product is not recommended in patients with a history of food aspiration. If barium studies are required in these patients or in patients in whom integrity of the swallowing mechanism is unknown, proceed with caution. If this product is aspirated into the larynx, further administration should be immediately discontinued.

After any barium study of the GI tract, it is important to rehydrate the patient as quickly as possible to prevent impaction of the bowel by barium sulfate. To prevent barium sulfate impaction in the bowel, the use of mild laxatives such as milk of magnesia or lactulose, following completion of the examination may also be required. These mild laxatives are recommended on a routine basis and in patients with a history of constipation unless contraindicated.

Oral Administration

Use with caution in patient with complete or nearly complete obstruction of the gastrointestinal tract.

Rectal Administration

Use with caution when obstructive lesions of the colon are suspected. Care should be taken to minimize the amount of barium sulfate allowed to flow proximal to obstructive lesions of the colon. When used rectally, care must be taken during insertion of the enema tip into the patient, since forceful or too deep insertion may cause tearing or perforation of the rectum.

Information for Patients

Before administration of this product patients should be instructed to:

1. Inform their physician if they are pregnant.
2. Inform their physician if they are allergic to any drugs or food, or if they have had any prior reactions to barium sulfate products or other contrast agents used in x-ray procedures (see PRECAUTIONS - General).
3. Inform their physician about any other medications they are currently taking.

Drug Interactions

The presence of barium sulfate formulations in the GI tract may alter the absorption of therapeutic agents taken concomitantly. In order to minimize any potential change in absorption, the separate administration of barium sulfate from that of other agents should be considered.

Usage in Pregnancy

Radiation is known to cause harm to the unborn fetus exposed in utero. Therefore, radiographic procedures should only be used when, in the judgement of the physician, their use is deemed essential to the welfare of the pregnant patient.

Nursing Mothers

Barium sulfate products may be used during lactation.

ADVERSE REACTIONS

Adverse reactions, such as nausea, vomiting, diarrhea and abdominal cramping, accompanying the use of barium sulfate formulations are infrequent and usually mild. Severe reactions (approximately 1 in 1,000,000) and fatalities (approximately 1 in 10,000,000) have occurred. Procedural complications are rare, but may include aspiration pneumonitis, barium sulfate impaction, granuloma formation, intravasation, embolization and peritonitis following intestinal perforation, vasovagal and syncopal episodes, and fatalities. EKG changes have been reported following or during barium enema procedures. It is of the utmost importance to be completely prepared to treat any such occurrence.

ALLERGIC REACTIONS

Due to the increased likelihood of allergic reactions in atopic patients, it is important that a complete history of known and suspected allergies as well as allergic-like symptoms, e.g., rhinitis, bronchial asthma, eczema and urticaria, must be obtained prior to any medical procedure utilizing these products. A mild allergic reaction would most likely include generalized pruritus, erythema or urticaria (approximately 1 in 250,000). Such reactions will generally respond to an antihistamine such as 50 mg of diphenhydramine or its equivalent. In the rarer, more serious reactions (approximately 1 in 1,000,000) laryngeal edema, bronchospasm or hypotension could develop. Severe reactions which may require emergency measures are often characterized by peripheral vasodilation, hypotension, reflex tachycardia, dyspnea, agitation, confusion and cyanosis progressing to unconsciousness. Treatment should be initiated immediately with 0.3 to 0.5 mL of 1:1000 epinephrine subcutaneously. If bronchospasm predominates, 0.25 to 0.50 grams of intravenous aminophylline should be given slowly. Appropriate vasopressors might be required. Adrenocorticosteroids, even if given intravenously, exert no significant effect on the acute allergic reactions for a few hours. The administration of these agents should not be regarded as emergency measures for the treatment of allergic reactions.

Apprehensive patients may develop weakness, pallor, tinnitus, diaphoresis and bradycardia following the administration of any diagnostic agent. Such reactions are usually non-allergic in nature and are best treated by having the patient lie flat for an additional 10 to 30 minutes under observation.

All E-Z-EM barium contrast and barium contrast delivery systems are latex-free. However, allergic reactions to enema accessories, in particular to retention catheters (tips) with latex cuffs, can occur. Such reactions could occur immediately and result in the previously mentioned acute allergic-like responses or might be delayed in appearance and result in a contact dermatitis. Known atopic patients, particularly those with a history of asthma or eczema, should be evaluated for alternative methods of administration in order to avoid these adverse reactions. All plastic/rubber accessories are disposable, single-use devices that must not be reused or left in the body cavity for an extended period of time.

OVERDOSAGE

On rare occasions following repeated administration, severe stomach cramps, nausea, vomiting, diarrhea or constipation may occur. These are transitory in nature and are not considered serious. Symptoms may be treated according to currently accepted standards of medical care.

DOSAGE AND ADMINISTRATION

General

The volume and concentration of LIQUID POLIBAR PLUS® to be administered will depend on the degree and extent of contrast required in the area(s) under examination and on the equipment and technique employed. See applicable system below for typical adult dose.

Patient Preparation for Colon Examinations

In order to achieve optimum results, the colon must be cleansed prior to the use of a barium enema. This is usually accomplished by placing the patient on a low fat, low residue diet, combined with the use of laxatives and/or cathartics. A cleansing enema may also be used unless contraindicated.

RECTAL ADMINISTRATION

In order to assure rapid colonic filling and drainage, LIQUID POLIBAR PLUS® should only be used with an enema kit with a large (½ inch) lumen such as the Super XL® Enema Bag System (Cat. No. 8925) or equivalent. Refer to the enema kit labeling for additional CONTRAINDICATIONS, WARNINGS, PRECAUTIONS, and INSTRUCTIONS FOR USE. Refer to manufacturer’s instructions if another administration system is used.

Single Contrast Colon Studies

Dilute 1 part LIQUID POLIBAR PLUS® with 5 parts water to yield approximately 17.5% w/v, 15% w/w; or dilute as required.
Typical Adult Dose: 1000 mL to 2500 mL of diluted suspension.

Double Contrast Colon Studies

Use undiluted.
Typical Adult Dose: 500 mL to 1500 mL or as directed by a physician.

ORAL ADMINISTRATION

Esophagus and Cardiac Series

Undiluted LIQUID POLIBAR PLUS® should be administered orally for double-contrast examination of the esophagus. Films are taken during rapid swallowing of barium sulfate.
Typical Adult Dose: 60 mL to 300 mL

Stomach

LIQUID POLIBAR PLUS® can be used for single or double-contrast examination of the stomach. It can be used undiluted or diluted 1:1 with water to produce a 52.5% w/v. Diluted LIQUID POLIBAR PLUS® is highly suited for a biphasic examination of the stomach. Following completion of the double-contrast examination of the stomach using E-Z-HD™ barium sulfate, undiluted or diluted 1:1 with water, LIQUID POLIBAR PLUS® may be used for the single phase of the study.
Typical Adult Dose: 150 mL to 340 mL of diluted or undiluted as applicable.

Small Bowel Series

LIQUID POLIBAR PLUS® can be used for small bowel series. It can be given alone or can be used following the completion of a double-contrast examination of the stomach using E-Z-HD™. It may be given either undiluted or in 1:1 dilution. Higher dilution will decrease the density of the barium sulfate but will increase the speed of the flow of contrast.
Typical Adult Dose: 340 mL to 750 mL of diluted or undiluted as applicable.

STORAGE

USP Controlled Room Temperature, 20 to 25°C (68 to 77°F). Protect from freezing.

HOW SUPPLIED

LIQUID POLIBAR PLUS® is supplied as follows:
750 mL jugs, NDC 32909-167-55.

Rx Only

SHAKE WELL PRIOR TO USE

Manufactured by
E-Z-EM Canada Inc.
for E-Z-EM, Inc.
a subsidiary of Bracco Diagnostics Inc.
Monroe Township, NJ 08831
Tel: 1-516-333-8230 1-800 544-4624
rev. 02/20 CL10F901

PACKAGE LABEL

Liquid Polibar Plus Bottle
NDC:32909-167-55